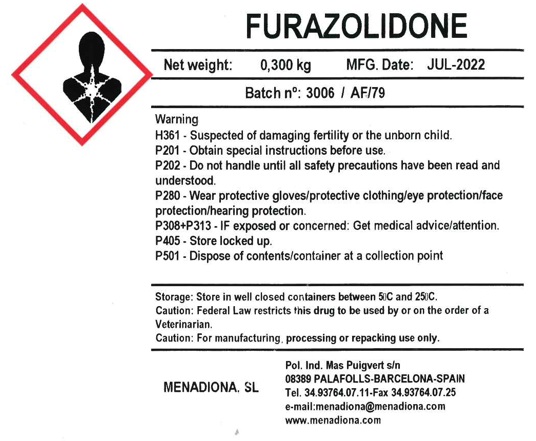 DRUG LABEL: Furazolidone
NDC: 17369-006 | Form: POWDER
Manufacturer: Menadiona, S.L.
Category: other | Type: BULK INGREDIENT - ANIMAL DRUG
Date: 20220901

ACTIVE INGREDIENTS: FURAZOLIDONE 1 kg/1 kg

PACKAGE LABEL

Furazolidone